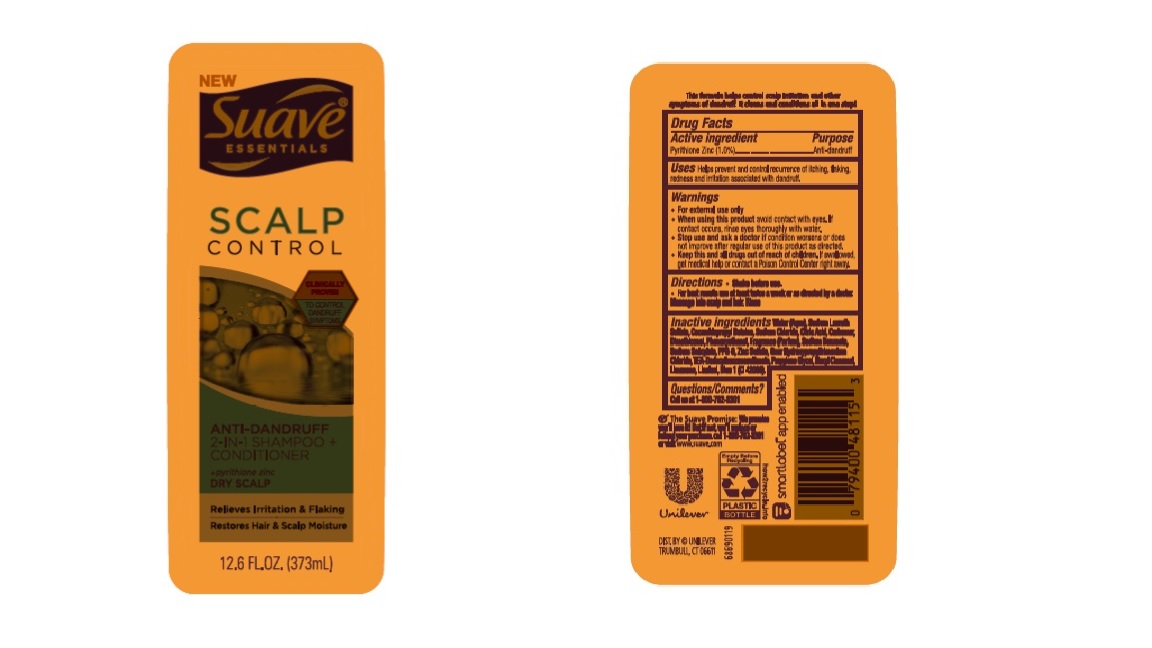 DRUG LABEL: Suave
NDC: 64942-2144 | Form: SHAMPOO
Manufacturer: Conopco, Inc. d/b/a/ Unilever
Category: otc | Type: HUMAN OTC DRUG LABEL
Date: 20230804

ACTIVE INGREDIENTS: PYRITHIONE ZINC 1 g/100 mL
INACTIVE INGREDIENTS: LINALOOL, (+/-)-; FD&C BLUE NO. 1; WATER; SODIUM LAURETH SULFATE; COCAMIDOPROPYL BETAINE; SODIUM CHLORIDE; DIMETHICONOL (40 CST); CARBOMER HOMOPOLYMER TYPE C (ALLYL PENTAERYTHRITOL CROSSLINKED); GUAR HYDROXYPROPYLTRIMONIUM CHLORIDE (1.7 SUBSTITUENTS PER SACCHARIDE); CITRIC ACID MONOHYDRATE; ZINC SULFATE, UNSPECIFIED FORM; TRIETHANOLAMINE DODECYLBENZENESULFONATE; PPG-9; PROPYLENE GLYCOL; .ALPHA.-HEXYLCINNAMALDEHYDE; LIMONENE, (+)-

Suave Essentials Scalp Control Anti-Dandruff 2-IN-1 Shampoo + Conditioner

Drug Facts

Active ingredient
Pyrithione Zinc (1.0%)

Purpose

Anti-dandruff

Use

Helps prevent and control recurrence of itching, flaking, redness and irritation associated with dandruff.

Warnings

For external use only

When using this product: avoid contact with eyes. If contact occurs, rinse eyes thoroughly with water.
Stop use and ask a doctor if: condition worsens or does not improve after regular use of this product as directed.

KEEP OUT OF REACH OF CHILDREN

Keep this and all drugs out of reach of children. If swallowed, get medical help or contact a Poison Control Center right away.

Directions

Shake before use.

For best results, use at least twice a week or as directed by a doctor.
Message into scalp and hair. Rinse

Inactive Ingredients

Water (Aqua), Sodium Laureth Sulfate, Cocamidopropyl Betaine, Sodium Chloride, Citric Acid, Carbomer, Dimethiconol, Phenoxyethanol, Fragrance (Parfum), Sodium Benzoate, Sodium Salicylate, PPG-9, Zinc Sulfate, Guar Hydroxypropyltrimonium Chloride, TEA-Dodecylbenzenesulfonate,

Questions/comments?

Call us at 1-800-782-8301